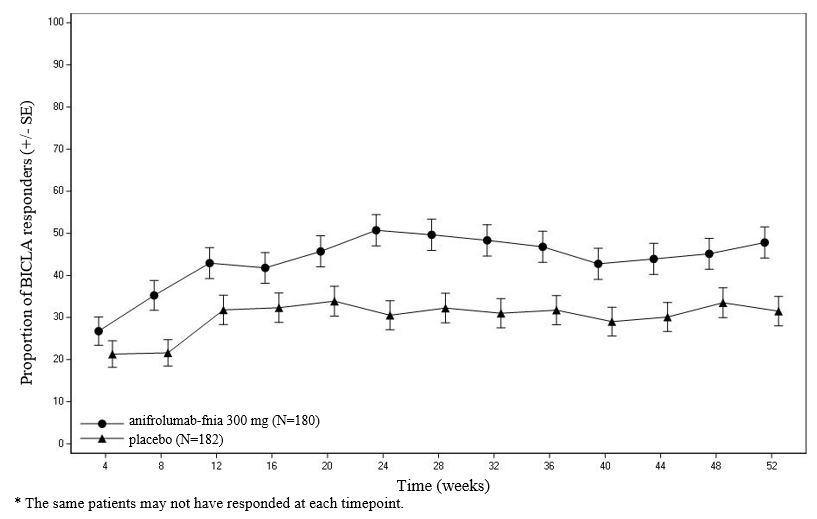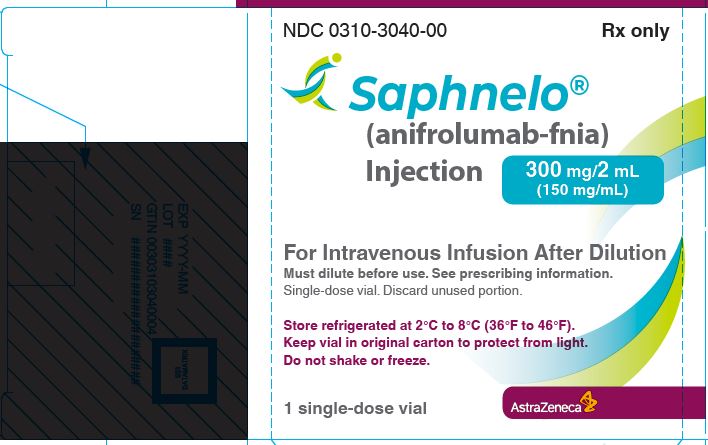 DRUG LABEL: SAPHNELO
NDC: 0310-3040 | Form: INJECTION, SOLUTION
Manufacturer: AstraZeneca Pharmaceuticals LP
Category: prescription | Type: HUMAN PRESCRIPTION DRUG LABEL
Date: 20240807

ACTIVE INGREDIENTS: ANIFROLUMAB 300 mg/2.0 mL
INACTIVE INGREDIENTS: HISTIDINE 3 mg/2.0 mL; HISTIDINE MONOHYDROCHLORIDE MONOHYDRATE 6 mg/2.0 mL; LYSINE HYDROCHLORIDE 18 mg/2.0 mL; TREHALOSE DIHYDRATE 98 mg/2.0 mL; POLYSORBATE 80 1 mg/2.0 mL; WATER

HIGHLIGHTS OF PRESCRIBING INFORMATION

These highlights do not include all the information needed to use SAPHNELO® safely and effectively. See full prescribing information for SAPHNELO.
SAPHNELO (anifrolumab-fnia) injection, for intravenous use
Initial U.S. Approval: 2021

RECENT MAJOR CHANGES

Warnings and Precautions, Serious Infections (5.1) 12/2023

1 INDICATIONS AND USAGE

SAPHNELO is a type I interferon (IFN) receptor antagonist indicated for the treatment of adult patients with moderate to severe systemic lupus erythematosus (SLE), who are receiving standard therapy. (1)

Limitations of Use: The efficacy of SAPHNELO has not been evaluated in patients with severe active lupus nephritis or severe active central nervous system lupus. Use of SAPHNELO is not recommended in these situations. (1)

2 DOSAGE AND ADMINISTRATION

The recommended dosage is 300 mg as an intravenous infusion over a 30‑minute period every 4 weeks. For complete dilution and intravenous administration instructions see Full Prescribing Information. (2.1)

3 DOSAGE FORMS AND STRENGTHS

Injection: 300 mg/2 mL (150 mg/mL) in a single-dose vial. (3)

4 CONTRAINDICATIONS

SAPHNELO is contraindicated in patients with a history of anaphylaxis with anifrolumab-fnia. (4)

5 WARNINGS AND PRECAUTIONS

- Serious Infections: Serious and sometimes fatal infections have occurred in patients receiving SAPHNELO. SAPHNELO increases the risk of respiratory infections and herpes zoster. Avoid initiating treatment during an active infection. Consider the individual benefit-risk if using in patients with severe or chronic infections. Consider interrupting therapy with SAPHNELO if patients develop a new infection during treatment. (5.1)
- Hypersensitivity Reactions Including Anaphylaxis: Serious hypersensitivity reactions including anaphylaxis and angioedema have been reported. (5.2)
- Malignancy: Consider the individual benefit-risk in patients with known risk factors for malignancy prior to prescribing SAPHNELO. (5.3)
- Immunizations: Avoid use of live or live-attenuated vaccines in patients receiving SAPHNELO. (5.4)
- Not Recommended for Use with Other Biologic Therapies. (5.5)

6 ADVERSE REACTIONS

Most common adverse drug reactions (incidence ≥5%) are nasopharyngitis, upper respiratory tract infections, bronchitis, infusion related reactions, herpes zoster and cough. (6)

To report SUSPECTED ADVERSE REACTIONS, contact AstraZeneca at 1-800-236-9933 or FDA at 1-800-FDA-1088 or www.fda.gov/medwatch.

FULL PRESCRIBING INFORMATION

1 INDICATIONS AND USAGE

SAPHNELO (anifrolumab-fnia) is indicated for the treatment of adult patients with moderate to severe systemic lupus erythematosus (SLE), who are receiving standard therapy [see Clinical Studies (14)].

Limitations of Use

The efficacy of SAPHNELO has not been evaluated in patients with severe active lupus nephritis or severe active central nervous system lupus. Use of SAPHNELO is not recommended in these situations.

2 DOSAGE AND ADMINISTRATION

2.1 Dosage Recommendations

SAPHNELO must be diluted prior to intravenous administration [see Dosage and Administration (2.2)].

The recommended dosage of SAPHNELO is 300 mg, administered as an intravenous infusion over a 30-minute period, every 4 weeks.

Missed dose

If a planned infusion is missed, administer SAPHNELO as soon as possible. Maintain a minimum interval of 14 days between infusions.

2.2 Instructions for Preparation and Administration

SAPHNELO is supplied as a single-dose vial. Prepare the diluted infusion solution using aseptic technique, by the following procedure:

1. Visually inspect the vial for particulate matter and discoloration. SAPHNELO is a clear to opalescent, colorless to slightly yellow, solution. Discard the vial if the solution is cloudy, discolored or visible particles are observed. Do not shake the vial.
2. Withdraw and discard 2 mL of solution from a 50 mL or 100 mL 0.9% Sodium Chloride Injection, USP infusion bag.
3. Withdraw 2 mL of solution from the vial of SAPHNELO and add it to the infusion bag. Mix the solution by gentle inversion. Do not shake.
4. Each vial is intended for one time use only. Discard any unused portion remaining in the vial.
5. Administer the infusion solution immediately after preparation.
6. If the infusion solution is not administered immediately, store the diluted solution of SAPHNELO at room temperature (59°F to 77°F, 15°C to 25°C) for up to 4 hours, or refrigerated (36°F to 46°F, 2°C to 8°C) for up to 24 hours. Do not freeze. Protect from light. If refrigerated, allow the diluted SAPHNELO solution to reach room temperature prior to administration.
7. Administer the infusion solution intravenously over a 30-minute period through an infusion line containing a sterile, low-protein binding 0.2 to 15 micron in-line or add-on filter.
8. To ensure the complete dose of SAPHNELO has been administered, flush the entire infusion line with 25 mL of 0.9% Sodium Chloride Injection, USP at the end of the infusion.
9. Do not co-administer other medicinal products through the same infusion line.
10. Dispose of any unused medicinal product or waste material in accordance with local requirements.

3 DOSAGE FORMS AND STRENGTHS

Injection: 300 mg/2 mL (150 mg/mL) as a clear to opalescent, colorless to slightly yellow, solution in a single-dose vial.

4 CONTRAINDICATIONS

SAPHNELO is contraindicated in patients with a history of anaphylaxis with anifrolumab-fnia [see Warnings and Precautions (5.2)].

5 WARNINGS AND PRECAUTIONS

5.1 Serious Infections

Serious and sometimes fatal infections (including COVID‑19) have occurred in patients receiving immunosuppressive agents, including SAPHNELO. Overall, the incidence of serious infections in controlled trials was similar in patients receiving SAPHNELO compared with placebo, whereas fatal infections occurred more frequently in patients receiving SAPHNELO [see Adverse Reactions (6.1)].

In controlled trials, SAPHNELO increased the risk of respiratory infections and herpes zoster (disseminated herpes zoster events have been reported) [see Adverse Reactions (6.1)].

Consider the benefit and risk of administering SAPHNELO in patients with a chronic infection, a history of recurrent infections, or known risk factors for infection. Avoid initiating treatment with SAPHNELO in patients with any clinically significant active infection until the infection resolves or is adequately treated. Instruct patients to seek medical advice if signs or symptoms of clinically significant infection occur. If a patient develops an infection, or is not responding to standard anti-infective therapy, monitor the patient closely and consider interrupting SAPHNELO therapy until the infection resolves.

5.2 Hypersensitivity Reactions Including Anaphylaxis

Serious hypersensitivity reactions (including anaphylaxis) have been reported following SAPHNELO administration [see Contraindication (4)]. Events of angioedema have also been reported [see Adverse Reactions (6.1)].

Other hypersensitivity reactions and infusion-related reactions have occurred following administration of SAPHNELO [see Adverse Reactions (6.1)]. Consider pre-medication before infusion of SAPHNELO for patients with a history of these reactions.

SAPHNELO should be administered by healthcare providers prepared to manage hypersensitivity reactions, including anaphylaxis, and infusion-related reactions. If a serious infusion-related or hypersensitivity reaction (e.g., anaphylaxis) occurs, immediately interrupt the administration of SAPHNELO and initiate appropriate therapy.

5.3 Malignancy

There is an increased risk of malignancies with the use of immunosuppressants. The impact of SAPHNELO treatment on the potential development of malignancies is not known.

Consider the individual benefit-risk in patients with known risk factors for the development or reoccurrence of malignancy prior to prescribing SAPHNELO. In patients who develop malignancies, consider the benefit-risk of continued treatment with SAPHNELO.

5.4 Immunizations

Update immunizations, according to current immunization guidelines, prior to initiating SAPHNELO therapy. Avoid concurrent use of live or live-attenuated vaccines in patients treated with SAPHNELO.

5.5 Not Recommended for Concomitant Use with Other Biologic Therapies

SAPHNELO has not been studied in combination with other biologic therapies, including B-cell-targeted therapies. Therefore, use of SAPHNELO is not recommended for use in combination with biologic therapies.

6 ADVERSE REACTIONS

The following clinically significant adverse reactions are also discussed elsewhere in the labeling:

- Serious Infections [see Warnings and Precautions (5.1)]
- Hypersensitivity Reactions Including Anaphylaxis [see Warnings and Precautions (5.2)]
- Malignancy [see Warnings and Precautions (5.3)]

6.1 Clinical Trials Experience

Because clinical trials are conducted under widely varying conditions, adverse reaction rates observed in the clinical trials of a drug cannot be directly compared to rates in the clinical trials of another drug and may not reflect the rates observed in practice.

The safety of SAPHNELO was assessed through 52 weeks in patients with moderate to severe SLE who received anifrolumab-fnia 300 mg by intravenous infusion every 4 weeks (N=459), compared to placebo (N=466) in controlled clinical trials (Trials 1, 2 and 3) [see Clinical Studies (14)]. The population studied had a mean age of 41 years (range: 18 to 69), of which 93% were female, 60% White, 13% Black/African American, and 10% Asian.

In the controlled-clinical trials, adverse reactions, irrespective of causality, were reported in 87% of patients receiving SAPHNELO and 79% of patients receiving placebo.

Adverse reactions that occurred at greater than or equal to 2% incidence are shown in Table 1.

Table 1 Adverse Reactions Occurring in ≥2% of Patients on SAPHNELO 300 mg (Trials 1, 2 and 3) at 52 weeks
Adverse Reaction | SAPHNELO; (N=459); % | Placebo; (N=466); %
Upper respiratory tract infection [Upper respiratory tract infections (including Upper respiratory tract infections, Nasopharyngitis, Pharyngitis)] | 34 | 23
Bronchitis [Bronchitis (including Bronchitis, Bronchitis viral, Tracheobronchitis)] | 11 | 5.2
Infusion‑related reactions | 9.4 | 7.1
Herpes Zoster | 6.1 | 1.3
Cough | 5.0 | 3.2
Respiratory tract infection [Respiratory tract infection (including Respiratory tract infection, Respiratory tract infection viral, Respiratory tract infection bacterial)] | 3.3 | 1.5
Hypersensitivity | 2.8 | 0.6
All patients received standard therapy.

Long-term Safety

Patients who completed Trials 2 and 3 (Phase III feeder trials) were eligible to continue on treatment in a randomized, double-blind, placebo-controlled long-term extension (LTE) study, for an additional 3 years. The long-term safety of SAPHNELO was assessed in 257 patients who received anifrolumab-fnia 300 mg and 112 patients who received placebo in both a feeder trial and the LTE. Of these, 177 patients who received SAPHNELO (68.9%) and 52 patients who received placebo (46.4%) completed a total of 4 years on treatment. The overall long-term safety profile of SAPHNELO was consistent with Trials 1, 2 and 3.

Specific Adverse Reactions

Infections

In the 52‑week controlled-clinical trials, infections were reported in a greater proportion of patients while on treatment with SAPHNELO compared to placebo (69.7% [320/459] versus 55.4% [258/466]), corresponding to exposure-adjusted incidence rates (EAIR) of 141.8 and 99.9 per 100 patient years (PY), respectively.

Serious Infections

In the 52‑week controlled-clinical trials, the incidence of serious infections while on treatment was 4.8% (22/459) in patients treated with SAPHNELO compared with 5.6% (26/466) in patients receiving placebo, corresponding to EAIR of 5.4 and 6.6 per 100 PY, respectively. The most frequent serious infection was pneumonia.

In the 52‑week controlled-clinical trials, fatal infections occurred in 0.4% of patients receiving SAPHNELO and 0.2% of the patients receiving placebo.

During the LTE study, the most common serious infections were COVID-19 and pneumonia.

Herpes Zoster

In the 52‑week controlled-clinical trials, the incidence of herpes zoster in patients while on treatment with SAPHNELO was 6.1% (28/459) and 1.3% (6/466) in patients on placebo, corresponding to EAIRs of 6.9 and 1.5 per 100 PY, respectively. Cases with multidermatomal involvement and disseminated presentation have been reported. Of the 28 SAPHNELO-treated patients with herpes zoster, 2 experienced disseminated disease requiring hospitalization compared to none among patients who received placebo.

Hypersensitivity Reactions Including Anaphylaxis

During the SLE development program, there was one report of an anaphylactic reaction in a patient who received 150 mg anifrolumab-fnia, and 4 reports of angioedema after 300 mg. In general, the hypersensitivity reactions were predominantly mild or moderate in intensity and did not lead to discontinuation of SAPHNELO.

In the 52‑week controlled-clinical trials, hypersensitivity reactions occurred in 2.8% (13/459) of patients while on treatment with SAPHNELO and 0.6% (3/466) of patients on placebo, corresponding to EAIR of 3.2 and 0.7 per 100 PY, respectively. Serious hypersensitivity reactions were reported for 0.6% (3/459) of patients receiving SAPHNELO, including angioedema (n=2).

Infusion-related Reactions

Infusion-related reactions were mild to moderate in intensity; the most common symptoms were headache, nausea, vomiting, fatigue, and dizziness.

In the 52‑week controlled-clinical trials, the incidence of infusion-related reactions while on treatment was 9.4% (43/459) in patients while on treatment with SAPHNELO and 7.1% (33/466) in patients on placebo, corresponding to EAIRs of 11.1 and 8.7 per 100 PY, respectively.

Malignancies

In 52‑week controlled-clinical trials, malignancies (excluding non-melanoma skin cancers) were observed in 0.7% (3/459) and 0.6% (3/466) of patients receiving SAPHNELO and placebo, corresponding to EAIR of 0.7 and 0.7 per 100 PY, respectively. Malignant neoplasm (including non-melanoma skin cancers) was reported for 1.3% (6/459) patients receiving SAPHNELO, compared to 0.6% (3/466) patients receiving placebo (EAIR: 1.3 and 0.7 per 100 PY, respectively). The malignancies that were reported in more than one patient treated with SAPHNELO included breast cancer and squamous cell carcinoma.

6.2 Postmarketing Experience

The following adverse reaction has been identified during post-approval use of SAPHNELO. Because the reactions are reported voluntarily from a population of uncertain size, it is not always possible to reliably estimate their frequency or establish a causal relationship to drug exposure.

Arthralgia

7 DRUG INTERACTIONS

No formal drug interaction studies have been conducted.

8 USE IN SPECIFIC POPULATIONS

8.1 Pregnancy

Pregnancy Exposure Registry

A pregnancy exposure registry monitors pregnancy outcomes in women exposed to SAPHNELO during pregnancy. For more information about the registry or to report a pregnancy while on SAPHNELO, contact AstraZeneca at 1‑877‑693‑9268.

Risk Summary

The limited human data with SAPHNELO use in pregnant women are insufficient to inform on drug-associated risk for major birth defects, miscarriage, or adverse maternal or fetal outcome. Monoclonal IgG antibodies are known to be actively transported across the placenta as pregnancy progresses; therefore, anifrolumab-fnia exposure to the fetus may be greater during the third trimester of pregnancy.

In an enhanced pre- and post-natal development study with pregnant cynomolgus monkeys that received intravenous administration of anifrolumab-fnia, there was no evidence of embryotoxicity or fetal malformations with exposures up to approximately 28‑times the exposure at the maximum recommended human dose (MRHD) on an Area Under Curve (AUC) basis (see Data).

All pregnancies have a background risk of birth defect, loss, or other adverse outcomes. The estimated background risk of major birth defects and miscarriage for the indicated population is unknown. In the U.S. general population, the estimated background risk of major birth defects and miscarriage in clinically recognized pregnancies is 2% to 4% and 15% to 20%, respectively.

Clinical Considerations

Disease-Associated Maternal and/or Embryo/Fetal Risk: Pregnant women with SLE are at increased risk of adverse pregnancy outcomes, including worsening of the underlying disease, premature birth, miscarriage, and intrauterine growth restriction. Maternal lupus nephritis increases the risk of hypertension and preeclampsia/eclampsia. Passage of maternal autoantibodies across the placenta may result in adverse neonatal outcomes, including neonatal lupus and congenital heart block.

Data

Animal Data: In an enhanced pre- and post-natal development study, pregnant cynomolgus monkeys received anifrolumab-fnia at intravenous doses of 30 or 60 mg/kg once every 2 weeks from confirmation of pregnancy at Gestation Day 20, throughout the gestation period, and continuing until 1‑month post-partum (approximately Lactation Day 28). There was no evidence of anifrolumab-fnia related maternal toxicity, embryo-fetal toxicity, or post-natal developmental effects. No anifrolumab-fnia related effect on T-cell-dependent antibody response in the infants was noted up to Day 180 after birth. The no observed adverse effect level (NOAEL) for maternal and developmental toxicity was identified as 60 mg/kg (approximately 28‑times the MRHD on an AUC basis). In the infants, mean serum concentrations of anifrolumab‑fnia on Day 30 after birth increased with dose and were approximately 4.2% to 9.7% of the respective maternal concentrations. The anifrolumab-fnia concentrations in the infant serum were up to approximately 22‑times the concentrations in the maternal milk, suggesting that anifrolumab-fnia had transferred via the placenta.

8.2 Lactation

Risk Summary

No data are available regarding the presence of SAPHNELO in human milk, the effects on the breastfed child, or the effects on milk production. Anifrolumab-fnia was detected in the milk of female cynomolgus monkeys administered anifrolumab-fnia. Due to species-species differences in lactation physiology, animal data may not reliably predict drug levels in humans. Maternal IgG is known to be present in human milk. If anifrolumab-fnia is transferred into human milk, the effects of local gastrointestinal exposure and limited systemic exposure in the breastfed infant to anifrolumab-fnia are unknown.

The developmental and health benefits of breastfeeding should be considered along with the mother's clinical need for anifrolumab-fnia and any potential adverse effects on the breast-fed child from anifrolumab-fnia or from the underlying maternal condition.

8.4 Pediatric Use

The safety and efficacy of SAPHNELO in pediatric patients less than 18 years of age have not been established.

8.5 Geriatric Use

Of the 664 patients with SLE exposed to anifrolumab-fnia in clinical trials, 3% (n=20) were 65 and over. The number of patients aged 65 years of age and older was not sufficient to determine whether they respond differently from younger adult patients.

11 DESCRIPTION

Anifrolumab-fnia is a type I interferon (IFN) receptor antagonist, immunoglobulin G1 kappa (IgG1κ) monoclonal antibody that is produced in mouse myeloma cells (NS0) by recombinant DNA technology. The molecular weight is approximately 148 kDa.

SAPHNELO (anifrolumab-fnia) injection is a sterile, preservative‑free, clear to opalescent, colorless to slightly yellow, solution for intravenous use. SAPHNELO contains anifrolumab-fnia at a concentration of 150 mg/mL in a single-dose vial.

Each vial contains 300 mg (150 mg/mL) of anifrolumab-fnia, L-histidine (3 mg), L-histidine hydrochloride monohydrate (6 mg), L-lysine hydrochloride (18 mg), polysorbate 80 (1 mg), trehalose dihydrate (98 mg), and Water for Injection, USP. The pH is 5.9.

12 CLINICAL PHARMACOLOGY

12.1 Mechanism of Action

Anifrolumab-fnia is a human IgG1κ monoclonal antibody that binds to subunit 1 of the type I interferon receptor (IFNAR) with high specificity and affinity. This binding inhibits type I IFN signaling, thereby blocking the biologic activity of type I IFNs. Anifrolumab-fnia also induces the internalization of IFNAR1, thereby reducing the levels of cell surface IFNAR1 available for receptor assembly. Blockade of receptor mediated type I IFN signaling inhibits IFN responsive gene expression as well as downstream inflammatory and immunological processes. Inhibition of type I IFN blocks plasma cell differentiation and normalizes peripheral T-cell subsets.

Type I IFNs play a role in the pathogenesis of SLE. Approximately 60-80% of adult patients with active SLE express elevated levels of type I IFN inducible genes.

12.2 Pharmacodynamics

In patients with SLE, following the administration of anifrolumab-fnia at 300 mg dose, via intravenous infusion every 4 weeks for 52 weeks, neutralization (≥80%) of a type I IFN gene signature was observed from Week 4 to Week 52 in blood samples of patients with elevated levels of type I IFN inducible genes and returned to baseline levels within 8 to 12 weeks following withdrawal of anifrolumab-fnia at the end of the 52-week treatment period. However, the clinical relevance of the type I IFN gene signature neutralization is unclear.

In SLE patients with positive anti-dsDNA antibodies at baseline (Trials 2 and 3), treatment with anifrolumab-fnia 300 mg led to numerical reductions in anti-dsDNA antibodies over time through Week 52.

In patients with low complement levels (C3 and C4), increases in complement levels were observed in patients receiving anifrolumab-fnia through Week 52.

12.3 Pharmacokinetics

The PK of anifrolumab-fnia was studied in adult patients with SLE following intravenous doses ranging from 100 to 1000 mg once every 4 weeks, and healthy volunteers following a single intravenous dose at 300 mg. Anifrolumab-fnia exhibits non-linear PK in the dose range of 100 mg to 1000 mg with more than dose-proportional increases in the exposure as measured by AUC. Following the 300 mg every 4 weeks intravenous administrations of anifrolumab-fnia, steady-state was reached by Day 85. The accumulation ratio was approximately 1.36 for Cmax and 2.49 for Ctrough.

Distribution

Based on population PK analysis, the estimated volume of distribution at steady state for a typical patient with SLE (69.1 kg) is 6.23 L.

Elimination

From population PK analysis, anifrolumab-fnia exhibited non-linear PK due to IFNAR1-mediated drug clearance.

Following the administration of anifrolumab-fnia at a dose of 300 mg via intravenous infusion every 4 weeks, the estimated systemic clearance (CL) for anifrolumab-fnia was 0.193 L/day.

Based on population PK analysis of patients who received SAPHNELO for one year, serum concentrations of anifrolumab-fnia were below detection in 95% of patients approximately 16 weeks after the last dose.

Specific Populations

There was no clinically meaningful difference in systemic clearance based on age, race, ethnicity, region, gender, IFN status or body weight, that requires dose adjustment.

Age: Based on population PK analyses, age (range 18 to 69 years) did not affect anifrolumab-fnia clearance. Limited PK data are available for elderly patients; 3% (n=20) of the patients included in the PK analysis were 65 years or older [see Use in Specific Populations (8.5)].

Renal Impairment: No specific clinical studies have been conducted to investigate the effect of renal impairment on anifrolumab-fnia. Based on population PK analyses, anifrolumab-fnia clearance was comparable in SLE patients with mild (60-89 mL/min/1.73 m^2) and moderate (30-59 mL/min/1.73 m^2) decrease in eGFR values and patients with normal renal function (≥90 mL/min/1.73 m^2). There were no SLE patients with a severe decrease in eGFR or end stage renal disease (<30 mL/min/1.73 m^2); anifrolumab-fnia is not cleared renally.

Patients with UPCR >2 mg/mg were excluded from the clinical trials. Based on population PK analyses, increased urine protein/creatinine ratio (UPCR) did not significantly affect anifrolumab-fnia clearance.

Hepatic Impairment: No specific clinical studies have been conducted to investigate the effect of hepatic impairment on anifrolumab-fnia. IgG1 monoclonal antibodies are predominantly eliminated via catabolism and are not expected to undergo hepatic metabolism; changes in hepatic function are not expected to influence anifrolumab-fnia clearance. Based on population PK analyses, baseline hepatic function biomarkers (ALT and AST ≤2.0 × ULN, and total bilirubin) had no clinically relevant effect on anifrolumab-fnia clearance.

Drug Interactions

No formal drug-drug interaction studies have been conducted.

Based on population PK analysis, concomitant use of oral corticosteroids, anti-malarials, immunosuppressants (azathioprine, methotrexate, mycophenolate mofetil, mycophenolic acid, and mizoribine), NSAIDs, ACE inhibitors, and HMG-CoA reductase inhibitors did not significantly affect the PK of anifrolumab-fnia.

12.6 Immunogenicity

The observed incidence of anti-drug antibodies is highly dependent on the sensitivity and specificity of the assay. Differences in assay methods preclude meaningful comparisons of the incidence of anti-drug antibodies in the studies described below with the incidence of anti-drug antibodies in other studies, including those of anifrolumab-fnia.

In Trials 2, 3, and the long-term extension, treatment emergent anti-anifrolumab-fnia antibodies were detected in 9 of 350 (ADA incidence 2.6%) patients who received SAPHNELO at the recommended dosing regimen for up to 4 years.

Because of the low occurrence of anti-drug antibodies, the effect of these antibodies on the pharmacokinetics, pharmacodynamics, safety, and/or effectiveness of anifrolumab-fnia products is unknown.

13 NONCLINICAL TOXICOLOGY

13.1 Carcinogenesis, Mutagenesis, Impairment of Fertility

The carcinogenic and genotoxic potential of anifrolumab-fnia have not been evaluated. In rodent models of IFNAR1 blockade, increased carcinogenic potential has been observed. The clinical relevance of these findings is unknown.

Effects on male and female fertility have not been directly evaluated in animal studies. No anifrolumab-fnia-related adverse effects on indirect measures of male or female fertility, based on semen analysis, spermatogenesis staging, menses cycle, organ weights and histopathological findings in the reproductive organs were observed in 9-month repeat-dose toxicity studies in cynomolgus monkeys at doses up to 50 mg/kg intravenous once weekly (approximately 58‑times the MRHD on an AUC basis).

14 CLINICAL STUDIES

The safety and efficacy of SAPHNELO were evaluated in three 52-week treatment period, multicenter, randomized, double-blind, placebo-controlled studies (Trial 1 [NCT01438489], Trial 2 [NCT02446912] and Trial 3 [NCT02446899]). Patients were diagnosed with SLE according to the American College of Rheumatology (1982 revised) classification criteria. All patients were ≥18 years of age and had moderate to severe disease, with a SLE Disease Activity Index 2000 (SLEDAI-2K) score ≥6 points, organ level involvement based on BILAG assessment, and a Physician’s Global Assessment [PGA] score ≥1, despite receiving standard SLE therapy consisting of either one or any combination of oral corticosteroids (OCS), antimalarials and/or immunosuppressants at baseline. Patients continued to receive their existing SLE therapy at stable doses during the clinical trials, with the exception of OCS (prednisone or equivalent) where tapering was a component of the protocol. Patients who had severe active lupus nephritis and patients who had severe active central nervous system lupus were excluded. The use of other biologic agents and cyclophosphamide were not permitted during the trials; patients receiving other biologic therapies were required to complete a wash-out period of at least 5 half‑lives prior to enrollment. All three studies were conducted in North America, Europe, South America and Asia. Patients received anifrolumab-fnia or placebo, administered by intravenous infusion, every 4 weeks.

Efficacy of SAPHNELO was established based on assessment of clinical response using the composite endpoints, the British Isles Lupus Assessment Group based Composite Lupus Assessment (BICLA) and the SLE Responder Index (SRI‑4).

BICLA response at Week 52, was defined as improvement in all organ domains with moderate or severe activity at baseline:

- Reduction of all baseline BILAG A to B/C/D and baseline BILAG B to C/D, and no BILAG worsening in other organ systems, as defined by ≥1 new BILAG A or ≥2 new BILAG B;
- No worsening from baseline in SLEDAI-2K, where worsening is defined as an increase from baseline of >0 points in SLEDAI-2K;
- No worsening from baseline in patients’ lupus disease activity, where worsening is defined by an increase ≥0.30 points on a 3-point PGA VAS;
- No discontinuation of treatment;
- No use of restricted medication beyond the protocol-allowed threshold.

SRI‑4 response, was defined as meeting each of the following criteria at Week 52 compared with baseline:

- Reduction from baseline of ≥4 points in the SLEDAI-2K;
- No new organ system affected as defined by 1 or more BILAG A or 2 or more BILAG B items compared to baseline;
- No worsening from baseline in the patients’ lupus disease activity defined by an increase ≥0.30 points on a 3‑point PGA visual analogue scale (VAS);
- No discontinuation of treatment;
- No use of restricted medication beyond the protocol-allowed threshold.

Trial 1 randomized 305 patients (1:1:1) who received anifrolumab-fnia, 300 mg or 1000 mg, or placebo for up to 52 weeks. The primary endpoint was a combined assessment of the SRI-4 and the sustained reduction in OCS (<10 mg/day and ≤OCS dose at week 1, sustained for 12 weeks) measured at Week 24.

Trial 2 and 3 were similar in design. Trial 2 randomized 457 patients who received anifrolumab-fnia 150 mg, 300 mg or placebo (1:2:2). Trial 3 randomized 362 patients (1:1) who received anifrolumab-fnia 300 mg or placebo. The primary endpoints were improvement in disease activity evaluated at 52 weeks, measured by SRI‑4 in Trial 2 and BICLA in Trial 3 (defined above). The common secondary efficacy endpoints included in both studies were the maintenance of OCS reduction, improvement in cutaneous SLE activity, and flare rate. During Weeks 8-40, patients with a baseline OCS ≥10 mg/day were required to taper their OCS dose to ≤7.5 mg/day, unless there was worsening of disease activity. Both studies evaluated the efficacy of anifrolumab-fnia 300 mg versus placebo; a dose of 150 mg was also evaluated for dose-response in Trial 2.

Patient demographics and disease characteristics were generally similar and balanced across treatment arms (Table 2).

Table 2 Demographics and Baseline Characteristics
 | Total Population
 | Trial 1; (N = 305) | Trial 2; (N = 457) | Trial 3; (N = 362)
Mean Age (years) | 40 | 41 | 42
Female (%) | 93 | 92 | 93
White (%) | 42 | 71 | 60
Black/African American (%) | 13 | 14 | 12
Asian (%) | 7 | 5 | 17
Hispanic or Latino (%) | 42 | 19 | 30
Baseline SLEDAI-2K score
Mean (SD) | 10.9 (4.1) | 11.3 (3.72) | 11.5 (3.76)
≥10 points, n (%) | 182 (60) | 328 (72) | 260 (72)
BILAG organ system scoring (Overall)
At least one A, n (%) | 152 (50) | 217 (48) | 176 (49)
No A and at least 2 Bs, n (%) | 134 (44) | 211 (46) | 169 (47)
Positive Anti-dsDNA levels, n (%) | 185 (77) | 207 (45) | 159 (44)
Abnormal ANA, n (%) | 299 (98) | 412 (90) | 325 (90)
Abnormal Complement C3 level, n (%) | 119 (39) | 157 (34) | 144 (40)
Abnormal Complement C4 level, n (%) | 74 (24) | 95 (21) | 95 (26)
Baseline SLE treatment
OCS, n (%) | 258 (85) | 381 (83) | 292 (81)
Antimalarials, n (%) | 219 (72) | 334 (73) | 252 (70)
Immunosuppressants, n (%) | 150 (49) | 214 (47) | 174 (48)

Randomization was stratified by disease severity (SLEDAI-2K score at baseline, <10 vs ≥10 points), OCS dose on Day 1 (<10 mg/day vs ≥10 mg/day prednisone or equivalent) and interferon gene signature test results (high vs low).

The reduction in disease activity seen in the BICLA and SRI-4 was related primarily to improvement in the mucocutaneous and musculoskeletal organ systems. Flare rate was reduced in patients receiving SAPHNELO compared to patients who received placebo although the difference was not statistically significant.

BICLA responder analysis: BICLA was the primary endpoint in Trial 3; anifrolumab-fnia 300 mg demonstrated statistically significant and clinically meaningful efficacy in overall disease activity compared with placebo, with greater improvements in all components of the composite endpoint. In Trial 1 and 2 BICLA was a pre-specified analysis. The BICLA results are presented in Table 3.

Table 3 BICLA Response Rate at Week 52
 | Trial 1 [Not formally tested in a pre-specified testing scheme and findings should be interpreted with caution.] [Based on post hoc analysis.] |  | Trial 2 |  | Trial 3 [Primary endpoint.]
 | Anifrolumab- fnia 300 mg; (N=99) | Placebo; (N=102) | Anifrolumab- fnia 300 mg; (N=180) | Placebo; (N=184) | Anifrolumab- fnia 300 mg; (N=180) | Placebo; (N=182)
BICLA Response Rate [In all 3 trials, patients who discontinued investigational product or initiated restricted medications beyond the protocol-specified thresholds are considered non-responders. For consistency, the results presented for Trial 2 represent the post-hoc analysis using the restricted medication thresholds as defined in Trial 3.]
Responder, n (%) | 54 (54.6) | 27 (25.8) | 85 (47.1) | 55 (30.2) | 86 (47.8) | 57 (31.5)
Difference in Response Rates (95% CI) | 28.8 (15.7, 41.9) |  | 17.0 (7.2, 26.8) |  | 16.3 (6.3, 26.3); p-value = 0.001
Components of BICLA Response
BILAG Improvement, n (%) | 54 (54.5) | 28 (27.5) | 85 (47.2) | 58 (31.5) | 88 (48.9) | 59 (32.4)
No Worsening of SLEDAI-2K, n (%) | 73 (73.7) | 61 (59.8) | 121 (67.2) | 104 (56.5) | 122 (67.8) | 94 (51.6)
No Worsening of PGA, n (%) | 76 (76.8) | 62 (60.8) | 117 (65.0) | 105 (57.1) | 122 (67.8) | 95 (52.2)
The response rates and associated difference and 95% CI are calculated using a Cochran-Mantel-Haenszel approach adjusted for stratification factors. The reported percentages for the components are unadjusted.

In Trial 3, examination of subgroups by age, race, gender, ethnicity, disease severity [SLEDAI-2K at baseline], and baseline OCS use did not identify differences in response to anifrolumab-fnia.

Figure 1 shows the proportion of BICLA responders through the 52-week treatment period in Trial 3.

Figure 1 Trial 3: Proportion (%) of BICLA Responders by Visit*

SRI-4 responder analysis: SRI-4 was the primary endpoint in Trial 2; treatment with anifrolumab-fnia did not result in statistically significant improvements over placebo. In Trials 1 and 3, SRI-4 was a pre-specified analysis. The SRI-4 results are presented in Table 4.

Table 4 SRI-4 Response Rate at Week 52
 | Trial 1 [Not formally tested in a pre-specified testing scheme and findings should be interpreted with caution.] |  | Trial 2 [Primary endpoint.] |  | Trial 3
 | Anifrolumab- fnia 300 mg; (N=99) | Placebo; (N=102) | Anifrolumab- fnia 300 mg; (N=180) | Placebo; (N=184) | Anifrolumab- fnia 300 mg; (N=180) | Placebo; (N=182)
SRI-4 Response Rate [In all 3 studies, patients who discontinued investigational product or initiated restricted medications beyond the protocol-specified thresholds are considered non-responders. For consistency, the results presented for Trial 2 represent the post-hoc analysis using the restricted medication thresholds as defined in Trial 3. The most commonly involved SLEDAI-2K organ domains were mucocutaneous, musculoskeletal and immune.]
Responder, n (%) | 62 (62.8) | 41 (38.8) | 88 (49.0) | 79 (43.0) | 100 (55.5) | 68 (37.3)
Difference in Response Rates (95% CI) | 24.0 (10.9, 37.2) |  | 6.0 (-4.2, 16.2) |  | 18.2 (8.1, 28.3)
Components of SRI-4 Response
SLEDAI-2K improvement, n (%) | 62 (62.6) | 41 (40.2) | 89 (49.4) | 80 (43.5) | 101 (56.1) | 71 (39.0)
No worsening of BILAG, n (%) | 75 (75.8) | 61 (59.8) | 119 (66.1) | 105 (57.1) | 125 (69.4) | 94 (51.6)
No worsening of PGA, n (%) | 76 (76.8) | 62 (60.8) | 117 (65.0) | 105 (57.1) | 122 (67.8) | 95 (52.2)
The response rates and associated difference and 95% CI are calculated using a Cochran-Mantel-Haenszel approach adjusted for stratification factors. The reported percentages for the components are unadjusted.

Effect on Concomitant Steroid Treatment: In Trial 3, among the 47% of patients with a baseline OCS use ≥10 mg/day, anifrolumab-fnia demonstrated a statistically significant difference in the proportion of patients able to reduce OCS use by at least 25% to ≤7.5 mg/day at Week 40 and maintain the reduction through Week 52 (p-value = 0.004); 52% (45/87) of patients in the anifrolumab-fnia group versus 30% (25/83) in the placebo achieved this level of steroid reduction (difference 21% [95% CI 6.8, 35.7]). Consistent trends in favor of anifrolumab-fnia compared to placebo, on effect of reduction of OCS use, were observed in Trial 1 and 2, but the difference was not statistically significant.

16 HOW SUPPLIED/STORAGE AND HANDLING

SAPHNELO (anifrolumab-fnia) injection is a sterile, preservative-free, clear to opalescent, colorless to slightly yellow solution for intravenous infusion. It is packaged in a 2 mL clear glass vial containing 300 mg/2 mL (150 mg/mL) of anifrolumab-fnia.

SAPHNELO is available in a carton containing one single-dose vial (NDC-0310-3040-00).

Store in a refrigerator at 36°F to 46°F (2°C to 8°C) in the original carton to protect from light.

Do not freeze. Do not shake.

17 PATIENT COUNSELING INFORMATION

Advise the patient to read the FDA-approved patient labeling (Patient Information).

Serious Infections

Inform patients that SAPHNELO may decrease their ability to fight infections, and that serious infections, including fatal ones, occurred in patients receiving SAPHNELO in clinical trials. Also inform patients that they are at increased risk of respiratory infections and herpes zoster during treatment with SAPHNELO [see Warnings and Precautions (5.1)]. Advise patients to contact their healthcare provider if they develop any symptoms of an infection, including fever or flu-like symptoms; muscle aches; cough; shortness of breath; burning when they urinate or urinating more often than usual; diarrhea or stomach pain; shingles (a red skin rash that can cause pain and burning).

Hypersensitivity Reactions/Anaphylaxis

Inform patients that serious hypersensitivity reactions, including anaphylaxis, have been reported in patients who received SAPHNELO. Instruct patients to immediately tell their healthcare provider or go to the emergency department of their nearest hospital, if they experience symptoms of an allergic reaction (e.g., anaphylaxis) during or after the administration of SAPHNELO [see Warnings and Precautions (5.2)]. Symptoms may include swelling of the face, tongue, or mouth, breathing difficulties, and/or fainting, dizziness, feeling lightheaded (due to a drop in blood pressure).

Immunizations

Inform patients that they should not receive live or live-attenuated vaccines while receiving SAPHNELO. Advise patients to discuss with their healthcare provider before seeking immunizations on their own [see Warnings and Precautions (5.4)].

Pregnancy

Advise female patients to inform their healthcare provider if they intend to become pregnant during therapy, suspect they are pregnant or become pregnant while receiving SAPHNELO [see Use in Specific Populations (8.1)].

Inform women that they can find information about a pregnancy exposure registry which monitors pregnancy outcomes in women exposed to SAPHNELO by calling AstraZeneca at 1-877-693-9268.

Manufactured by: AstraZeneca AB Södertälje, Sweden SE-15185

US License No. 2059

Distributed by: AstraZeneca Pharmaceuticals LP, Wilmington, DE 19850

©AstraZeneca 2024

PATIENT INFORMATION

SAPHNELO® (saf-NEH-low)

(anifrolumab-fnia)

injection, for intravenous use

What is SAPHNELO?

- SAPHNELO is a prescription medicine used to treat adults with moderate to severe systemic lupus erythematosus (SLE or lupus) who are receiving other lupus medicines.
- SAPHNELO contains anifrolumab-fnia which is in a group of medicines called monoclonal antibodies. Lupus is a disease of the immune system (the body system that fights infection). When given together with other medicines for lupus, SAPHNELO may help to reduce your lupus disease activity more than other lupus medicines alone.
- It is not known if SAPHNELO is effective in people with severe active lupus nephritis or central nervous system lupus.
- It is not known if SAPHNELO is safe and effective in children under 18 years of age.

Do not use SAPHNELO if you:

- are allergic to anifrolumab-fnia or any of the ingredients in SAPHNELO. See the end of this Patient Information leaflet for a complete list of ingredients in SAPHNELO.

Before you receive SAPHNELO, tell your healthcare provider about all of your medical conditions, including if you:

- think you have an infection or have infections that keep coming back. You should not receive SAPHNELO if you have an infection unless your healthcare provider tells you to. See “What are the possible side effects of SAPHNELO?”
- are scheduled to receive a vaccination or if you think you may need a vaccination. You should not receive live vaccines during treatment with SAPHNELO.
- have or have had any type of cancer.
- are receiving other biologic medicines or monoclonal antibodies.
- are pregnant or plan to become pregnant. It is not known if SAPHNELO will harm your unborn baby. Tell your healthcare provider if you are pregnant, think you might be pregnant, or plan to become pregnant during your treatment with SAPHNELO.
  ∘ Pregnancy Exposure Registry. If you become pregnant while receiving SAPHNELO, talk to your healthcare provider. A pregnancy exposure registry monitors pregnancy outcomes in women exposed to SAPHNELO. You can find out more information about the registry by calling AstraZeneca at 1-877-693-9268.
- are breastfeeding or plan to breastfeed. It is not known if SAPHNELO passes into your breast milk. Talk to your healthcare provider about the best way to feed your baby while receiving SAPHNELO.

Tell your healthcare provider about all the medicines you take, including prescription and over-the-counter medicines, vitamins, and herbal supplements. SAPHNELO may affect the way other medicines work, and other medicines may affect how SAPHNELO works.

How will I receive SAPHNELO?

- Your healthcare provider will give you SAPHNELO through a needle placed in a vein (IV or intravenous infusion). It takes about 30 minutes to give you the full dose of SAPHNELO.
- SAPHNELO is usually given 1 time every 4 weeks.
- If you miss an appointment, call your healthcare provider as soon as possible to reschedule your appointment.

What are the possible side effects of SAPHNELO?

SAPHNELO may cause serious side effects, including:

- Serious Infections. SAPHNELO can lower the ability of your immune system to fight infections. You may be at a higher risk of developing respiratory infections, and shingles (herpes zoster) during treatment with SAPHNELO. Infections (including COVID-19) could be serious, leading to hospitalization or death. Tell your healthcare provider right away if you have any of the following symptoms of an infection:

- fever, sweating, or chills
- muscle aches
- cough
- shortness of breath

- burning when urinating
- urinating more often
- diarrhea or stomach pain
- warm, red, or painful skin or sores on your body.

- Allergic (hypersensitivity) reactions, including anaphylaxis. Serious allergic reactions can happen during or after you get your SAPHNELO infusion. Tell your healthcare provider or get emergency help right away if you have any of the following symptoms of a serious allergic reaction:

- swelling of your face, mouth, and tongue
- breathing problems

- fainting or dizziness
- feeling lightheaded (low blood pressure)

- Cancer. SAPHNELO may reduce the activity of your immune system. Medicines that affect the immune system may increase your risk of certain cancers.

The most common side effects of SAPHNELO include:

  - upper respiratory infections
  - infusion reactions
  - cough

- bronchitis
- shingles (herpes zoster)

These are not all of the possible side effects of SAPHNELO.

Call your doctor for medical advice about side effects. You may report side effects to FDA at 1‑800‑FDA‑1088.

General information about the safe and effective use of SAPHNELO

Medicines are sometimes prescribed for purposes other than those listed in a Patient Information leaflet. If you would like more information about SAPHNELO, talk with your healthcare provider. You can ask your pharmacist or healthcare provider for information about SAPHNELO that is written for health professionals.

What are the ingredients in SAPHNELO?

Active ingredient: anifrolumab-fnia

Inactive ingredients: L-histidine, L-histidine hydrochloride monohydrate, L-lysine hydrochloride, trehalose dihydrate, polysorbate 80 and Water for Injection.

Manufactured by: AstraZeneca AB Södertälje, Sweden SE-15185

Distributed by: AstraZeneca Pharmaceuticals LP, Wilmington, DE 19850

©AstraZeneca 2023

For more information, go to https://www.SAPHNELO.com or call 1-800-236-9933.

This Patient Information has been approved by the U.S. Food and Drug Administration.

Revised: December 2023

PACKAGE/LABEL PRINCIPAL DISPLAY PANEL – 300mg/2mL (150 mg/mL)

NDC 0310-3040-00 Rx only

SAPHNELO®

(anifrolumab-fnia)

Injection

300 mg/2 mL

(150 mg/mL)

For Intravenous Infusion After Dilution

Must dilute before use. See prescribing information.

Single-dose vial. Discard unused portion.

Store refrigerated at 2°C to 8°C (36°F to 46°F).

Keep vial in original carton to protect from light.

Do not shake or freeze.

1 single-dose vial

AstraZeneca